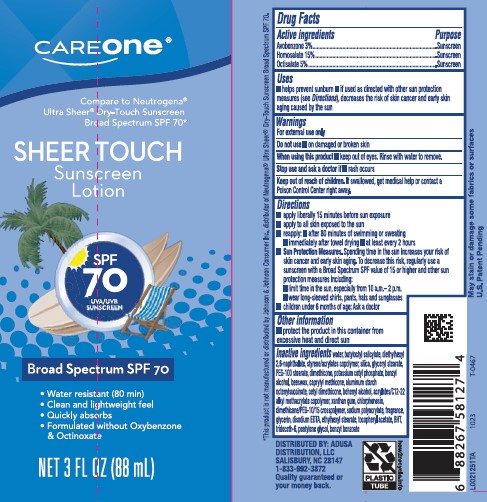 DRUG LABEL: Sheer Touch Sunscreen SPF 70
NDC: 72476-935 | Form: LOTION
Manufacturer: Retail Business Services, LLC
Category: otc | Type: HUMAN OTC DRUG LABEL
Date: 20260206

ACTIVE INGREDIENTS: AVOBENZONE 30 mg/1 mL; HOMOSALATE 150 mg/1 mL; OCTISALATE 50 mg/1 mL
INACTIVE INGREDIENTS: WATER; BUTYLOCTYL SALICYLATE; DIETHYLHEXYL 2,6-NAPHTHALATE; BUTYL ACRYLATE/METHYL METHACRYLATE/METHACRYLIC ACID COPOLYMER (18000 MW); SILICON DIOXIDE; GLYCERYL MONOSTEARATE; PEG-100 STEARATE; DIMETHICONE; POTASSIUM CETYL PHOSPHATE; BENZYL ALCOHOL; YELLOW WAX; CAPRYLYL TRISILOXANE; ALUMINUM STARCH OCTENYLSUCCINATE; CETYL DIMETHICONE 150; DOCOSANOL; BUTYL ACRYLATE/C16-C20 ALKYL METHACRYLATE/METHACRYLIC ACID/METHYL METHACRYLATE COPOLYMER; XANTHAN GUM; CHLORPHENESIN; DIMETHICONE/PEG-10/15 CROSSPOLYMER; SODIUM POLYACRYLATE (8000 MW); GLYCERIN; EDETATE DISODIUM ANHYDROUS; ETHYLHEXYL STEARATE; .ALPHA.-TOCOPHEROL ACETATE; BUTYLATED HYDROXYTOLUENE; TRIDECETH-6; PENTYLENE GLYCOL; BENZYL BENZOATE

Care One D35.000/D35AA
Sheer Touch Sunscreen SPF 70

Active ingredients

Avobenzone 3%

Homosalate 15%

Octisalate 5%

Purpose

Sunscreen

Uses

- helps prevent sunburn
- if used as directed with other sun protection measures (See Directions), decreases the risk of skin cancer and early skin aging caused by the sun

Warnings

For external use only

Do not use

- on damaged or broken skin

When using this product

- keep out of eyes. Rinse with water to remove.

Stop use and ask a doctor if

- rash occurs

Keep out of reach of children.

If swallowed, get medical help or contact a Poison Control right away.

Directions

- apply liberaly 15 minutes before sun exposure
- apply to all skin exposed to the sun
- reapply:
- after 80 minutes of swimming or sweating
- immediately after towel drying
- at least every 2 hours
- Sun Protection Measures. Spending time in the sun increases your risk of skin cancer and early skin aging. To decrease this risk, regularly use a sunscreen with Broad Spectrum SPF value of 15 or higher and other sun protection measures including:
- limit time in the sun, especialy from 10 a.m.-2 p.m.
- wear long-sleeved shirts, pants, hats and sunglasses
- children under 6 months of age: Ask a doctor

Other information

- protect the product in this container from excessive heat and direct sun

Inactive ingredients

water, butyloctyl salicylate, diethylhexyl 2,6-naphthalate, styrene/acrylates copolymer, silica, glyceryl stearate, PEG-100 stearate, dimethicone, potassium cetyl phosphate, benzyl alcohol, beeswax, caprylyl methicone, aluminum starch octenylsuccinate, cetyl dimethicone, behenyl alcohol, acrylates/C12-22 alkyl methacrylate copolymer, xanthan gum, chlorphenesin, dimethicone/PEG-10/15 crosspolymer, sodium polyacrylate, fragrance, glycerin, disodium EDTA, ethylhexyl stearate, tocopheryl acetate, BHT, trideceth-6, pentylene glycol, benzyl benzoate

Disclaimers

*This product is not manufactured or distributed by Johnson & Johnson Consumer, Inc., distributor of Neutrogena®Ultra Sheer®Dry-Touch Sunscreen Broad Spectrum SPF 70.

May stain or damage some fabrics or surfaces

U.S. Patent Pending

Adverse Reaction

DISTRIBUTED BY: ADUSA DISTRIBUTION, LLC

SALISBURY, NC 28147

1-833-922-3872

Quality guaranteed or your money back.

PLASTIC TUBE

how2recycle.info

Principal display panel

CAREone®

Compare to Neutrogena®Ultra Sheer®Dry-Touch Sunscreen Broad Spectrum SPF 70*

SHEER TOUCH

Sunscreen Lotion

SPF 70

UVA/UVB SUNSCREEN

Broad Spectrum SPF 70

- Water resistant (80 min)
- Clean and lightweight feel
- Quickly absorbs
- Formulated without Oxybenzone & Octinoxate

NET 3 FL OZ (88 mL)